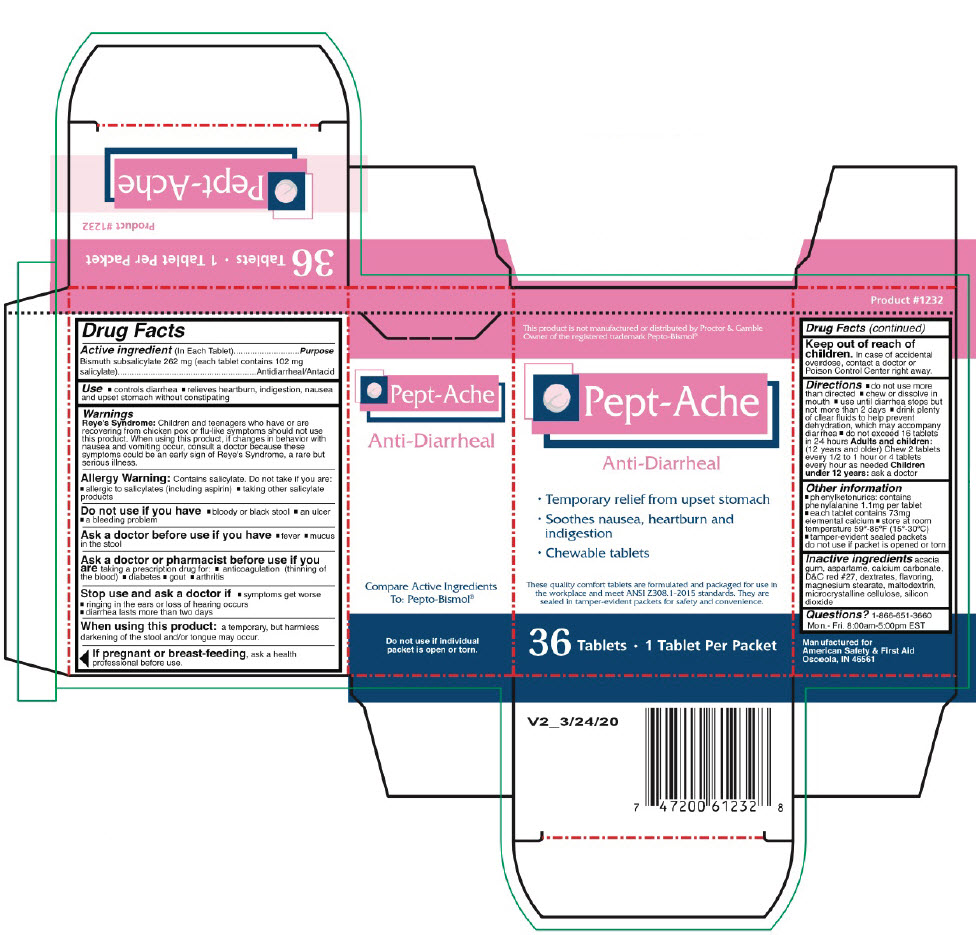 DRUG LABEL: PEPT-ACHE
NDC: 73598-1232 | Form: TABLET, CHEWABLE
Manufacturer: JHK Inc dba American Safety & First Aid
Category: otc | Type: HUMAN OTC DRUG LABEL
Date: 20240424

ACTIVE INGREDIENTS: BISMUTH SUBSALICYLATE 262 mg/1 1
INACTIVE INGREDIENTS: ACACIA; ASPARTAME; CALCIUM CARBONATE; D&C RED NO. 27; DEXTRATES; MAGNESIUM STEARATE; MALTODEXTRIN; MICROCRYSTALLINE CELLULOSE; SILICON DIOXIDE

PEPT-ACHE

Drug Facts

Active ingredient (In Each Tablet)

Bismuth subsalicylate 262 mg (each tablet contains 102 mg salicylate)

Purpose

Antidiarrheal/Antacid

Use

temporarily relieves:

- controls diarrhea
- relieves heartburn, indigestion, nausea and upset stomach without constipating

Warnings

Reye's Syndrome

Children and teenagers who have or are recovering from chicken pox or flu-like symptoms should not use this product. When using this product, if changes in behavior with nausea and vomiting occur, consult a doctor because these symptoms could be an early sign of Reye's Syndrome, a rare but serious illness.

Allergy Warning

Contains salicylate. Do not take if you are:

- allergic to salicylates (including aspirin)
- taking other salicylate products

Do not use if you have

- bloody or black stool
- an ulcer
- a bleeding problem

Ask a doctor before use if you have

- fever
- mucus in the stool

Ask a doctor or pharmacist before use if you are taking a prescription drug for:

- anticoagulation (thinning of the blood)
- diabetes
- gout
- arthritis

Stop use and ask a doctor if

- symptoms get worse
- ringing in the ears or loss of hearing occurs
- diarrhea lasts more than two days

When using this product: a temporary, but harmless darkening of the stool and/or tongue may occur.

PREGNANCY OR BREAST FEEDING

If pregnant or breast-feeding, ask a health professional before use.

Keep out of reach of children. In case of accidental overdose, contact a doctor or Poison Control Center right away.

Directions

- do not use more than directed
- chew or dissolve in mouth
- use until diarrhea stops but not more than 2 days
- drink plenty of clear fluids to help prevent dehydration, which may accompany diarrhea
- do not exceed 16 tablets in 24 hours Adults and children: (12 years and older) Chew 2 tablets every 1/2 to 1 hour or 4 tablets every hour as needed

Children under 12 years: ask a doctor

Other information

- phenylketonurics: contains phenylalanine 1.1mg per tablet
- each tablet contains 73mg elemental calcium
- store at room temperature 59º-86ºF (15º-30ºC)
- tamper-evident sealed packets do not use if packet is opened or torn

Inactive ingredients

acacia gum, aspartame, calcium carbonate, D&C red #27, dextrates, flavoring, magnesium stearate, maltodextrin, microcrystalline cellulose, silicon dioxide

Questions?

1-866-651-3660 Monday-Friday 8:00am-5:00pm EST

PRINCIPAL DISPLAY PANEL - 36 Tablet Packet Box

This product is not manufactured or distributed by Proctor & Gamble
Owner of the registered trademark Pepto-Bismol®.

Pept-Ache

Anti-Diarrheal

- Temporary relief from upset stomach
- Soothes nausea, heartburn and
  indigestion
- Chewable tablets

These quality comfort tablets are formulated and packaged for use in
the workplace and meet ANSI Z308. 1-2015 standards. They are
sealed in tamper-evident packets for safety and convenience.

36 Tablets • 1 Tablet Per Packet